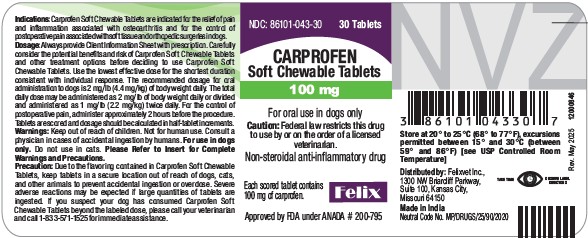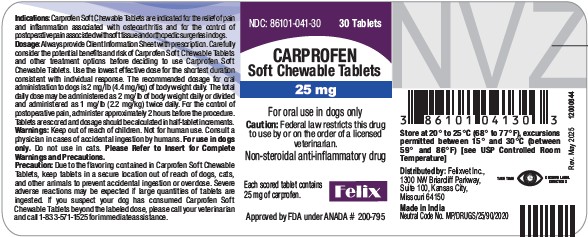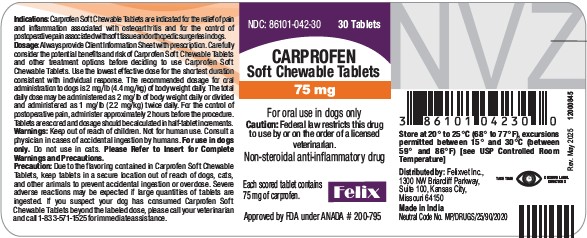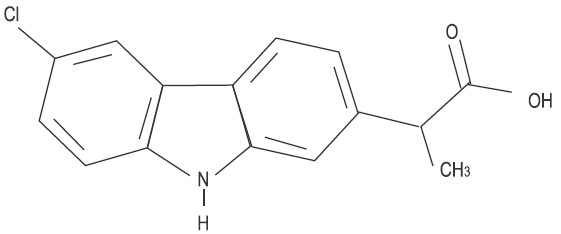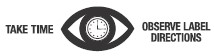 DRUG LABEL: Carprofen
NDC: 86101-041 | Form: TABLET
Manufacturer: FELIX PHARMACEUTICALS PRIVATE LIMITED
Category: animal | Type: Prescription Animal Drug Label
Date: 20260224

ACTIVE INGREDIENTS: CARPROFEN 25 mg/1 1

CARPROFEN
Soft Chewable Tablets
Non-steroidal anti-inflammatory drug
For oral use in dogs only

CAUTION

Federal law restricts this drug to use by or on the order of a licensed veterinarian.

DESCRIPTION

Carprofen Soft Chewable Tablets are a non-steroidal anti-inflammatory drug (NSAID) of the propionic acid class that includes ibuprofen, naproxen, and ketoprofen. Carprofen is the nonproprietary designation for a substituted carbazole, 6-chloro-α-methyl-9H-carbazole-2-acetic acid. The empirical formula is C15H12ClNO2 and the molecular weight 273.72. The chemical structure of carprofen is:

Carprofen is a white, crystalline compound. It is freely soluble in ethanol, but practically insoluble in water at 25°C.

CLINICAL PHARMACOLOGY

Carprofen is a non-narcotic, non-steroidal anti-inflammatory agent with characteristic analgesic and antipyretic activity approximately equipotent to indomethacin in animal models.^1

The mechanism of action of carprofen, like that of other NSAIDs, is believed to be associated with the inhibition of cyclooxygenase activity. Two unique cyclooxygenases have been described in mammals.^2 The constitutive cyclooxygenase, COX-1, synthesizes prostaglandins necessary for normal gastrointestinal and renal function. The inducible cyclooxygenase, COX-2, generates prostaglandins involved in inflammation. Inhibition of COX-1 is thought to be associated with gastrointestinal and renal toxicity while inhibition of COX-2 provides anti-inflammatory activity. The specificity of a particular NSAID for COX-2 versus COX-1 may vary from species to species.^3 In an in vitro study using canine cell cultures, carprofen demonstrated selective inhibition of COX-2 versus COX-1.^4 Clinical relevance of these data has not been shown. Carprofen has also been shown to inhibit the release of several prostaglandins in two inflammatory cell systems: rat polymorphonuclear leukocytes (PMN) and human rheumatoid synovial cells, indicating inhibition of acute (PMN system) and chronic (synovial cell system) inflammatory reactions.^1

Several studies have demonstrated that carprofen has modulatory effects on both humoral and cellular immune responses.^5-9 Data also indicate that carprofen inhibits the production of osteoclast-activating factor (OAF), PGE1, and PGE2 by its inhibitory effect in prostaglandin biosynthesis.^1

Based upon comparison with data obtained from intravenous administration, carprofen is rapidly and nearly completely absorbed (more than 90% bioavailable) when administered orally.^10 Peak blood plasma concentrations are achieved in 1-3 hours after oral administration of 1, 5, and 25 mg/kg to dogs. The mean terminal half-life of carprofen is approximately 8 hours (range 4.5-9.8 hours) after single oral doses varying from 1-35 mg/kg of body weight. After a 100 mg single intravenous bolus dose, the mean elimination half-life was approximately 11.7 hours in the dog. Carprofen is more than 99% bound to plasma protein and exhibits a very small volume of distribution.

Carprofen is eliminated in the dog primarily by biotransformation in the liver followed by rapid excretion of the resulting metabolites (the ester glucuronide of carprofen and the ether glucuronides of 2 phenolic metabolites, 7-hydroxy carprofen and 8-hydroxy carprofen) in the feces (70-80%) and urine (10-20%). Some enterohepatic circulation of the drug is observed.

INDICATIONS

Carprofen Soft Chewable Tablets are indicated for the relief of pain and inflammation associated with osteoarthritis and for the control of postoperative pain associated with soft tissue and orthopedic surgeries in dogs.

CONTRAINDICATIONS

Carprofen Soft Chewable Tablets should not be used in dogs exhibiting previous hypersensitivity to carprofen.

WARNINGS

Keep out of reach of children. Not for human use. Consult a physician in cases of accidental ingestion by humans. For use in dogs only. Do not use in cats.

All dogs should undergo a thorough history and physical examination before initiation of NSAID therapy. Appropriate laboratory tests to establish hematological and serum biochemical baseline data prior to, and periodically during, administration of any NSAID should be considered. Owners should be advised to observe for signs of potential drug toxicity (see Information for Dog Owners, Adverse Reactions, Animal Safety and Post-Approval Experience).

PRECAUTIONS

As a class, cyclooxygenase inhibitory NSAIDs may be associated with gastrointestinal, renal and hepatic toxicity. Effects may result from decreased prostaglandin production and inhibition of the enzyme cyclooxygenase which is responsible for the formation of prostaglandins from arachidonic acid.^11-14 When NSAIDs inhibit prostaglandins that cause inflammation they may also inhibit those prostaglandins which maintain normal homeostatic function. These anti-prostaglandin effects may result in clinically significant disease in patients with underlying or pre-existing disease more often than in healthy patients.^12,14 NSAID therapy could unmask occult disease which has previously been undiagnosed due to the absence of apparent clinical signs. Patients with underlying renal disease for example, may experience exacerbation or decompensation of their renal disease while on NSAID therapy.^11-14 The use of parenteral fluids during surgery should be considered to reduce the potential risk of renal complications when using NSAIDs perioperatively.

Carprofen is an NSAID, and as with others in that class, adverse reactions may occur with its use. The most frequently reported effects have been gastrointestinal signs. Events involving suspected renal, hematologic, neurologic, dermatologic, and hepatic effects have also been reported. Patients at greatest risk for renal toxicity are those that are dehydrated, on concomitant diuretic therapy, or those with renal, cardiovascular, and/or hepatic dysfunction. Concurrent administration of potentially nephrotoxic drugs should be approached cautiously, with appropriate monitoring. Concomitant use of Carprofen Soft Chewable Tablets with other anti-inflammatory drugs, such as other NSAIDs or corticosteroids, should be avoided because of the potential increase of adverse reactions, including gastrointestinal ulcerations and/or perforations. Sensitivity to drug-associated adverse reactions varies with the individual patient. Dogs that have experienced adverse reactions from one NSAID may experience adverse reactions from another NSAID. Carprofen treatment was not associated with renal toxicity or gastrointestinal ulceration in well-controlled safety studies of up to ten times the dose in healthy dogs.

Carprofen is not recommended for use in dogs with bleeding disorders (e.g., Von Willebrand's disease), as safety has not been established in dogs with these disorders. The safe use of carprofen in animals less than 6 weeks of age, pregnant dogs, dogs used for breeding purposes, or in lactating bitches has not been established. Studies to determine the activity of carprofen when administered concomitantly with other protein-bound or similarly metabolized drugs have not been conducted. Drug compatibility should be monitored closely in patients requiring additional therapy. Such drugs commonly used include cardiac, anticonvulsant and behavioral medications. It has been suggested that treatment with carprofen may reduce the level of inhalant anesthetics needed.^15

If additional pain medication is warranted after administration of the total daily dose of Carprofen Soft Chewable Tablets, alternative analgesia should be considered. The use of another NSAID is not recommended. Consider appropriate washout times when switching from one NSAID to another or when switching from corticosteroids use to NSAID use.

Due to the flavoring contained in Carprofen Soft Chewable Tablets, keep tablets in a secure location out of reach of dogs, cats, and other animals to prevent accidental ingestion or overdose. Severe adverse reactions may occur if large quantities of tablets are ingested. If you suspect your dog has consumed Carprofen Soft Chewable Tablets above the labeled dose, please call your veterinarian for immediate assistance and notify Felix Pharmaceuticals Private Limited at 1-833-571-1525.

INFORMATION FOR DOG OWNERS

Carprofen Soft Chewable Tablets, like other drugs of their class, are not free from adverse reactions. Owners should be advised of the potential for adverse reactions and be informed of the clinical signs associated with drug intolerance. Adverse reactions may include decreased appetite, vomiting, diarrhea, dark or tarry stools, increased water consumption, increased urination, pale gums due to anemia, yellowing of gums, skin or white of the eye due to jaundice, lethargy, incoordination, seizure, or behavioral changes. Serious adverse reactions associated with this drug class can occur without warning and in rare situations result in death (see Adverse Reactions). Owners should be advised to discontinue Carprofen Soft Chewable Tablets therapy and contact their veterinarian immediately if signs of intolerance are observed. The vast majority of patients with drug related adverse reactions have recovered when the signs are recognized, the drug is withdrawn, and veterinary care, if appropriate, is initiated. Owners should be advised of the importance of periodic follow up for all dogs during administration of any NSAID.

ADVERSE REACTIONS

During investigational studies for the caplet formulation with twice daily administration of 1 mg/lb, no clinically significant adverse reactions were reported. Some clinical signs were observed during field studies (n=297) which were similar for carprofen caplet- and placebo-treated dogs. Incidences of the following were observed in both groups: vomiting (4%), diarrhea (4%), changes in appetite (3%), lethargy (1.4%), behavioral changes (1%), and constipation (0.3%). The product vehicle served as control.

There were no serious adverse events reported during clinical field studies with once daily administration of 2 mg/lb. The following categories of abnormal health observations were reported. The product vehicle served as control.

Percentage of Dogs with Abnormal Health Observations Reported in Clinical Field Study
(2 mg/lb once daily)
Observation | Carprofen (n=129) | Placebo (n=132)
Inappetence | 1.6 | 1.5
Vomiting | 3.1 | 3.8
Diarrhea/Soft stool | 3.1 | 4.5
Behavior change | 0.8 | 0.8
Dermatitis | 0.8 | 0.8
PU/PD | 0.8 | --
SAP increase | 7.8 | 8.3
ALT increase | 5.4 | 4.5
AST increase | 2.3 | 0.8
BUN increase | 3.1 | 1.5
Bilirubinuria | 16.3 | 12.1
Ketonuria | 14.7 | 9.1

Clinical pathology parameters listed represent reports of increases from pre-treatment values; medical judgment is necessary to determine clinical relevance.

During investigational studies of surgical pain for the caplet formulation, no clinically significant adverse reactions were reported. The product vehicle served as control.

Percentage of Dogs with Abnormal Health Observations Reported in Surgical Pain Field Studies with Caplets (2 mg/lb once daily)
Observation* | Carprofen (n=148) | Placebo (n=149)
Vomiting | 10.1 | 13.4
Diarrhea/soft stool | 6.1 | 6.0
Ocular disease | 2.7 | 0
Inappetence | 1.4 | 0
Dermatitis/Skin lesion | 2.0 | 1.3
Dysrhythmia | 0.7 | 0
Apnea | 1.4 | 0
Oral/Periodontal disease | 1.4 | 0
Pyrexia | 0.7 | 1.3
Urinary tract disease | 1.4 | 1.3
Wound drainage | 1.4 | 0

*A single dog may have experienced more than one occurrence of an event.

During investigational studies for the chewable tablet formulation, gastrointestinal signs were observed in some dogs. These signs included vomiting and soft stools.

Post-Approval Experience:

Although not all adverse reactions are reported, the following adverse reactions are based on voluntary post-approval adverse drug experience reporting. The categories of adverse reactions are listed in decreasing order of frequency by body system.

Gastrointestinal: Vomiting, diarrhea, constipation, inappetence, melena, hematemesis, gastrointestinal ulceration, gastrointestinal bleeding, pancreatitis.

Hepatic: Inappetence, vomiting, jaundice, acute hepatic toxicity, hepatic enzyme elevation, abnormal liver function test(s), hyperbilirubinemia, bilirubinuria, hypoalbuminemia. Approximately one-fourth of hepatic reports were in Labrador Retrievers.

Neurologic: Ataxia, paresis, paralysis, seizures, vestibular signs, disorientation.

Urinary: Hematuria, polyuria, polydipsia, urinary incontinence, urinary tract infection, azotemia, acute renal failure, tubular abnormalities including acute tubular necrosis, renal tubular acidosis, glucosuria.

Behavioral: Sedation, lethargy, hyperactivity, restlessness, aggressiveness.

Hematologic: Immune-mediated hemolytic anemia, immune-mediated thrombocytopenia, blood loss anemia, epistaxis.

Dermatologic: Pruritus, increased shedding, alopecia, pyotraumatic moist dermatitis (hot spots), necrotizing panniculitis/vasculitis, ventral ecchymosis.

Immunologic or hypersensitivity: Facial swelling, hives, erythema.

In rare situations, death has been associated with some of the adverse reactions listed above.

CONTACT INFORMATION

Contact Felix Pharmaceuticals Private Limited at 1-833-571-1525. To report suspected adverse drug experiences, contact Felix Pharmaceuticals Private Limited at 1-833-571-1525. For additional information about reporting adverse drug experiences for animal drugs, contact FDA at 1-888-FDA-VETS or http://www.fda.gov/reportanimalae

To obtain a Safety Data Sheet(s), contact Felix Pharmaceuticals Private Limited at 1-833-571-1525.

DOSAGE AND ADMINISTRATION

Always provide Client Information Sheet with prescription. Carefully consider the potential benefits and risk of Carprofen Soft Chewable Tablets and other treatment options before deciding to use Carprofen Soft Chewable Tablets. Use the lowest effective dose for the shortest duration consistent with individual response. The recommended dosage for oral administration to dogs is 2 mg/lb of body weight daily. The total daily dose may be administered as 2 mg/lb of body weight once daily or divided and administered as 1 mg/lb twice daily. For the control of postoperative pain, administer approximately 2 hours before the procedure. Carprofen Soft Chewable Tablets are scored and dosage should be calculated in half-tablet increments. Tablets can be halved by placing the tablet on a hard surface and pressing down on both sides of the score. Carprofen Soft Chewable Tablets may be fed by hand or placed in food. Care should be taken to ensure that the dog consumes the complete dose.

EFFECTIVENESS

Confirmation of the effectiveness of carprofen for the relief of pain and inflammation associated with osteoarthritis, and for the control of postoperative pain associated with soft tissue and orthopedic surgeries, was demonstrated in 5 placebo-controlled, masked studies examining the anti-inflammatory and analgesic effectiveness of carprofen caplets in various breeds of dogs.

Separate placebo-controlled, masked, multicenter field studies confirmed the anti-inflammatory and analgesic effectiveness of carprofen caplets when dosed at 2 mg/lb once daily or when divided and administered at 1 mg/lb twice daily. In these 2 field studies, dogs diagnosed with osteoarthritis showed statistically significant overall improvement based on lameness evaluations by the veterinarian and owner observations when administered carprofen at labeled doses.

Separate placebo-controlled, masked, multicenter field studies confirmed the effectiveness of carprofen caplets for the control of postoperative pain when dosed at 2 mg/lb once daily in various breeds of dogs. In these studies, dogs presented for ovariohysterectomy, cruciate repair and aural surgeries were administered carprofen preoperatively and for a maximum of 3 days (soft tissue) or 4 days (orthopedic) postoperatively. In general, dogs administered carprofen showed statistically significant reduction in pain scores compared to controls.

ANIMAL SAFETY

Laboratory studies in unanesthetized dogs and clinical field studies have demonstrated that carprofen is well tolerated in dogs after oral administration.

In target animal safety studies, carprofen was administered orally to healthy Beagle dogs at 1, 3, and 5 mg/lb twice daily (1, 3 and 5 times the recommended total daily dose) for 42 consecutive days with no significant adverse reactions. Serum albumin for a single female dog receiving 5 mg/lb twice daily decreased to 2.1 g/dL after 2 weeks of treatment, returned to the pretreatment value (2.6 g/dL) after 4 weeks of treatment, and was 2.3 g/dL at the final 6-week evaluation. Over the 6-week treatment period, black or bloody stools were observed in 1 dog (1 incident) treated with 1 mg/lb twice daily and in 1 dog (2 incidents) treated with 3 mg/lb twice daily. Redness of the colonic mucosa was observed in 1 male that received 3 mg/lb twice daily.

Two of 8 dogs receiving 10 mg/lb orally twice daily (10 times the recommended total daily dose) for 14 days exhibited hypoalbuminemia. The mean albumin level in the dogs receiving this dose was lower (2.38 g/dL) than each of 2 placebo control groups (2.88 and 2.93 g/dL, respectively). Three incidents of black or bloody stool were observed in 1 dog. Five of 8 dogs exhibited reddened areas of duodenal mucosa on gross pathologic examination. Histologic examination of these areas revealed no evidence of ulceration, but did show minimal congestion of the lamina propria in 2 of the 5 dogs.

In separate safety studies lasting 13 and 52 weeks, respectively, dogs were administered orally up to 11.4 mg/lb/day (5.7 times the recommended total daily dose of 2 mg/lb) of carprofen. In both studies, the drug was well tolerated clinically by all of the animals. No gross or histologic changes were seen in any of the treated animals. In both studies, dogs receiving the highest doses had average increases in serum L-alanine aminotransferase (ALT) of approximately 20 IU.

In the 52-week study, minor dermatologic changes occurred in dogs in each of the treatment groups but not in the control dogs. The changes were described as slight redness or rash and were diagnosed as non-specific dermatitis. The possibility exists that these mild lesions were treatment related, but no dose relationship was observed.

Clinical field studies were conducted with 549 dogs of different breeds at the recommended oral doses for 14 days (297 dogs were included in a study evaluating 1 mg/lb twice daily and 252 dogs were included in a separate study evaluating 2 mg/lb once daily). In both studies the drug was clinically well tolerated and the incidence of clinical adverse reactions for carprofen-treated animals was no higher than placebo-treated animals (placebo contained inactive ingredients found in carprofen tablets). For animals receiving 1 mg/lb twice daily, the mean post-treatment serum ALT values were 11 IU greater and 9 IU less than pre-treatment values for dogs receiving carprofen and placebo, respectively. Differences were not statistically significant. For animals receiving 2 mg/lb once daily, the mean post-treatment serum ALT values were 4.5 IU greater and 0.9 IU less than pre-treatment values for dogs receiving carprofen and placebo, respectively. In the latter study, 3 carprofen-treated dogs developed a 3-fold or greater increase in (ALT) and/or (AST) during the course of therapy. One placebo-treated dog had a greater than 2-fold increase in ALT. None of these animals showed clinical signs associated with laboratory value changes. Changes in the clinical laboratory values (hematology and clinical chemistry) were not considered clinically significant. The 1 mg/lb twice daily course of therapy was repeated as needed at 2-week intervals in 244 dogs, some for as long as 5 years.

Clinical field studies were conducted in 297 dogs of different breeds undergoing orthopedic or soft tissue surgery. Dogs were administered 2 mg/lb of carprofen two hours prior to surgery then once daily, as needed for 2 days (soft tissue surgery) or 3 days (orthopedic surgery). Carprofen was well tolerated when used in conjunction with a variety of anesthetic-related drugs. The type and severity of abnormal health observation in carprofen- and placebo-treated animals were approximately equal and few in number (see Adverse Reactions). The most frequent abnormal health observation was vomiting and was observed at approximately the same frequency in carprofen- and placebo-treated animals. Changes in clinicopathologic indices of hematopoietic, renal, hepatic, and clotting function were not clinically significant. The mean post-treatment serum ALT values were 7.3 IU and 2.5 IU less than pre-treatment values for dogs receiving carprofen and placebo, respectively. The mean post-treatment AST values were 3.1 IU less for dogs receiving carprofen and 0.2 IU greater for dogs receiving placebo.

STORAGE

Store at 20° to 25°C (68° to 77° F), excursions permitted between 15° and 30°C (59° and 86°F) [see USP Controlled Room Temperature]

HOW SUPPLIED

Carprofen Soft Chewable Tablets contain 25 mg, 75 mg, or 100 mg of carprofen per tablet.

Carprofen Soft Chewable Tablets are available as:

25 mg tablets: yellowish brown to dark yellowish brown, mottled, rounded, and square-shaped tablets that have a scoreline on one side and are plain on the other side.

75 mg tablets: reddish brown to dark reddish brown, mottled, and octagonal tablets that have a scoreline on one side and are plain on the other side.

100 mg tablets: brown to dark brown, mottled, rounded, and square-shaped tablets that are debossed with the letter "C" on one side and have a scoreline on the other side.

Each tablet size is packaged in bottles containing 30 tablets.

NDC Number | Tablet Size | Tablets/Bottle
86101-041-30 | 25 mg | 30
86101-042-30 | 75 mg | 30
86101-043-30 | 100 mg | 30

REFERENCES

1. Baruth H, et al: In Anti-Inflammatory and Anti-Rheumatic Drugs, Vol. II, Newer Anti-Inflammatory Drugs, Rainsford KD, ed. CRC Press, Boca Raton, p. 33, 1986.

2. Vane JR, Botting RM: Mechanism of action of anti-inflammatory drugs. Scand J Rheumatol 25:102, pp. 9-21.

3. Grossman CJ, Wiseman J, Lucas FS, et al: Inhibition of constitutive and inducible cyclooxygenase activity in human platelets and mononuclear cells by NSAIDs and COX-2 inhibitors. Inflammation Research 44:253-257, 1995.

4. Ricketts AP, Lundy KM, Seibel SB: Evaluation of selective inhibition of canine cyclooxygenase 1 and 2 by carprofen and other nonsteroidal anti-inflammatory drugs. Am J Vet Res 59:11, pp. 1441-1446, November 1998.

5. Ceuppens JL, et al: Non-steroidal anti-inflammatory agents inhibit the synthesis of IgM rheumatoid factor in vitro. Lancet 1:528, 1982.

6. Ceuppens JL, et al: Endogenous prostaglandin E2 enhances polyclonal immunoglobulin production by ionically inhibiting T suppressor cell activity. Cell Immunol 70:41, 1982.

7. Schleimer RP, et al: The effects of prostaglandin synthesis inhibition on the immune response. Immunopharmacology 3:205, 1981.

8. Leung KH, et al: Modulation of the development of cell mediated immunity: possible roles of the products of cyclooxygenase and lipoxygenase pathways of arachidonic acid metabolism. Int J Immunopharmacology 4:195, 1982.

9. Veit BC: Immunoregulatory activity of cultured-induced suppressor macrophages. Cell Immunol 72: 14, 1982.

10. Schmitt M, et al: Biopharmaceutical evaluation of carprofen following single intravenous, oral, and rectal doses in dogs. Biopharm Drug Dispos 11(7):585, 1990.

11. Kore AM: Toxicology of nonsteroidal anti-inflammatory drugs. Veterinary Clinics of North America, Small Animal Practice 20, March 1990.

12. Binns SH: Pathogenesis and pathophysiology of ischemic injury in cases of acute renal failure. Compend for Cont Ed 16:1, January 1994.

13. Boothe DM: Prostaglandins: Physiology and clinical implications. Compend for Cont Ed 6:11, November 1984.

14. Rubin SI: Nonsteroidal anti-inflammatory drugs, prostaglandins, and the kidney. JAVMA 188:9, May 1986.

15. Ko CH, Lange DN, Mandsager RE, et al: Effects of butorphanol and carprofen on the minimal alveolar concentration of isoflurane in dogs. JAVMA 217:1025-1028, 2000.

Approved by FDA under ANADA # 200-795

Distributed by:

Felixvet Inc.,
1300 NW Briarcliff Parkway, Suite 100,
Kansas City, Missouri 64150

Made in India

Neutral Code No. MP/DRUGS/25/90/2020

Rev. May 2025

Dog Owner Information about

CARPROFEN Soft Chewable Tablets for Osteoarthritis and Post-Surgical Pain

This summary contains important information about Carprofen Soft Chewable Tablets. You should read this information before you start giving your dog Carprofen Soft Chewable Tablets and review it each time the prescription is refilled. This sheet is provided only as a summary and does not take the place of instructions from your veterinarian. Talk to your veterinarian if you do not understand any of this information or if you want to know more about Carprofen Soft Chewable Tablets.

What are Carprofen Soft Chewable Tablets?

Carprofen Soft Chewable Tablets are a nonsteroidal anti-inflammatory drug (NSAID) that is used to reduce pain and inflammation (soreness) due to osteoarthritis and pain following surgery in dogs. Carprofen Soft Chewable Tablets are a prescription drug for dogs. They are available as a soft chewable tablet and are given to dogs by mouth.

Osteoarthritis (OA) is a painful condition caused by "wear and tear" of cartilage and other parts of the joints that may result in the following changes or signs in your dog:

- Limping or lameness
- Decreased activity or exercise (reluctance to stand, climb stairs, jump or run, or difficulty in performing these activities)
- Stiffness or decreased movement of joints

To control surgical pain (e.g. for surgeries such as spays, ear procedures or orthopedic repairs) your veterinarian may administer Carprofen Soft Chewable Tablets before the procedure and recommend that your dog be treated for several days after going home.

What kind of results can I expect when my dog is on Carprofen Soft Chewable Tablets?

While Carprofen Soft Chewable Tablets are not a cure for osteoarthritis, they can relieve the pain and inflammation of OA and improve your dog's mobility.

- Response varies from dog to dog but can be quite dramatic.
- In most dogs, improvement can be seen in a matter of days.
- If Carprofen Soft Chewable Tablets are discontinued or not given as directed, your dog's pain and inflammation may come back.

Who should not take Carprofen Soft Chewable Tablets?

Your dog should not be given Carprofen Soft Chewable Tablets if he/she:

- Has had an allergic reaction to carprofen, the active ingredient of Carprofen Soft Chewable Tablets.
- Has had an allergic reaction to aspirin or other NSAIDs (for example deracoxib, etodolac, firocoxib, meloxicam, phenylbutazone or tepoxalin) such as hives, facial swelling, or red or itchy skin.

Carprofen Soft Chewable Tablets should be given to dogs only. Cats should not be given Carprofen Soft Chewable Tablets. Call your veterinarian immediately if your cat receives Carprofen Soft Chewable Tablets. People should not take Carprofen Soft Chewable Tablets. Keep Carprofen Soft Chewable Tablets and all medicines out of reach of children. Call your physician immediately if you accidently take Carprofen Soft Chewable Tablets.

How to give Carprofen Soft Chewable Tablets to your dog.

Carprofen Soft Chewable Tablets should be given according to your veterinarian's instructions. Your veterinarian will tell you what amount of Carprofen Soft Chewable Tablets is right for your dog and for how long it should be given. Most dogs will take Carprofen Soft Chewable Tablets right out of your hand or the tablet can be placed in the mouth. Carprofen Soft Chewable Tablets may be given with or without food.

What to tell/ask your veterinarian before giving Carprofen Soft Chewable Tablets.

Talk to your veterinarian about:

- The signs of OA you have observed (for example limping, stiffness).
- The importance of weight control and exercise in the management of OA.
- What tests might be done before Carprofen Soft Chewable Tablets are prescribed.
- How often your dog may need to be examined by your veterinarian.
- The risks and benefits of using Carprofen Soft Chewable Tablets.

Tell your veterinarian if your dog has ever had the following medical problems:

- Experienced side effects from Carprofen Soft Chewable Tablets or other NSAIDs, such as aspirin
- Digestive upset (vomiting and/or diarrhea)
- Liver disease
- Kidney disease
- A bleeding disorder (for example, Von Willebrand's disease)

Tell your veterinarian about:

- Any other medical problems or allergies that your dog has now or has had.
- All medicines that you are giving your dog or plan to give your dog, including those you can get without a prescription.

Tell your veterinarian if your dog is:

- Pregnant, nursing or if you plan to breed your dog.

What are the possible side effects that may occur in my dog during Carprofen Soft Chewable Tablets therapy?

Carprofen Soft Chewable Tablets, like other drugs, may cause some side effects. Serious but rare side effects have been reported in dogs taking NSAIDs, including Carprofen Soft Chewable Tablets. Serious side effects can occur with or without warning and in rare situations result in death.

The most common NSAID-related side effects generally involve the stomach (such as bleeding ulcers), and liver or kidney problems. Look for the following side effects that can indicate your dog may be having a problem with Carprofen Soft Chewable Tablets or may have another medical problem:

- Decrease or increase in appetite
- Vomiting
- Change in bowel movements (such as diarrhea, or black, tarry or bloody stools)
- Change in behavior (such as decreased or increased activity level, incoordination, seizure or aggression)
- Yellowing of gums, skin, or whites of the eyes (jaundice)
- Change in drinking habits (frequency, amount consumed)
- Change in urination habits (frequency, color, or smell)
- Change in skin (redness, scabs, or scratching)

It is important to stop therapy and contact your veterinarian immediately if you think your dog has a medical problem or side effect from Carprofen Soft Chewable Tablets therapy. If you have additional questions about possible side effects, talk to your veterinarian.

Can Carprofen Soft Chewable Tablets be given with other medicines?

Carprofen Soft Chewable Tablets should not be given with other NSAIDs (for example, aspirin, deracoxib, etodolac, firocoxib, meloxicam, tepoxalin) or steroids (for example, cortisone, dexamethasone, prednisone, triamcinolone). Tell your veterinarian about all medicines you have given your dog in the past, and any medicines that you are planning to give with Carprofen Soft Chewable Tablets. This should include other medicines that you can get without a prescription. Your veterinarian may want to check that all of your dog's medicines can be given together.

What do I do in case my dog eats more than the prescribed amount of Carprofen Soft Chewable Tablets?

Contact your veterinarian immediately if your dog eats more than the prescribed amount of Carprofen Soft Chewable Tablets.

How to store Carprofen Soft Chewable Tablets.

Carprofen Soft Chewable Tablets are designed to taste good to animals.

Keep Carprofen Soft Chewable Tablets in a secure location out of reach of dogs, cats, and other animals to prevent accidental ingestion or overdose. If your dog ingests more than your veterinarian prescribed, or if your other pets take Carprofen Soft Chewable Tablets, contact your veterinarian right away.

What else should I know about Carprofen Soft Chewable Tablets?

This sheet provides a summary of information about Carprofen Soft Chewable Tablets. If you have any questions or concerns about Carprofen Soft Chewable Tablets or osteoarthritis pain, or postoperative pain, talk to your veterinarian. As with all prescribed medicines, Carprofen Soft Chewable Tablets should only be given to the dog for which they were prescribed. They should be given to your dog only for the condition for which they were prescribed. It is important to periodically discuss your dog's response to Carprofen Soft Chewable Tablets at regular check ups. Your veterinarian will best determine if your dog is responding as expected and if your dog should continue receiving Carprofen Soft Chewable Tablets.

Contact Felix Pharmaceuticals Private Limited at 1-833-571-1525. To report suspected adverse drug experiences, contact Felix Pharmaceuticals Private Limited at 1-833-571-1525. For additional information about reporting adverse drug experiences for animal drugs, contact FDA at 1-888-FDA-VETS or http://www.fda.gov/reportanimalae

To obtain a Safety Data Sheet(s), contact Felix Pharmaceuticals Private Limited at 1-833-571-1525.

Approved by FDA under ANADA # 200-795

Distributed by:

Felixvet Inc.,
1300 NW Briarcliff Parkway, Suite 100,
Kansas City, Missouri 64150

Made in India

Neutral Code No. MP/DRUGS/25/90/2020

Rev. May 2025

PACKAGE LABEL.PRINCIPAL DISPLAY PANEL

NDC: 86101-041-30 30 Tablets

CARPROFEN

Soft Chewable Tablets

25 mg

For oral use in dogs only

Caution: Federal law restricts this drug to use by or on the order of a licensed veterinarian.

Non-steroidal anti-inflammatory drug

Each scored tablets contains 25 mg of carprofen.

Approved by FDA under ANADA # 200-795

PACKAGE LABEL.PRINCIPAL DISPLAY PANEL

NDC: 86101-042-30 30 Tablets

CARPROFEN

Soft Chewable Tablets

75 mg

For oral use in dogs only

Caution: Federal law restricts this drug to use by or on the order of a licensed veterinarian.

Non-steroidal anti-inflammatory drug

Each scored tablets contains 75 mg of carprofen.

Approved by FDA under ANADA # 200-795

PACKAGE LABEL.PRINCIPAL DISPLAY PANEL

NDC: 86101-043-30 30 Tablets

CARPROFEN

Soft Chewable Tablets

100 mg

For oral use in dogs only

Caution: Federal law restricts this drug to use by or on the order of a licensed veterinarian.

Non-steroidal anti-inflammatory drug

Each scored tablets contains 100 mg of carprofen.

Approved by FDA under ANADA # 200-795